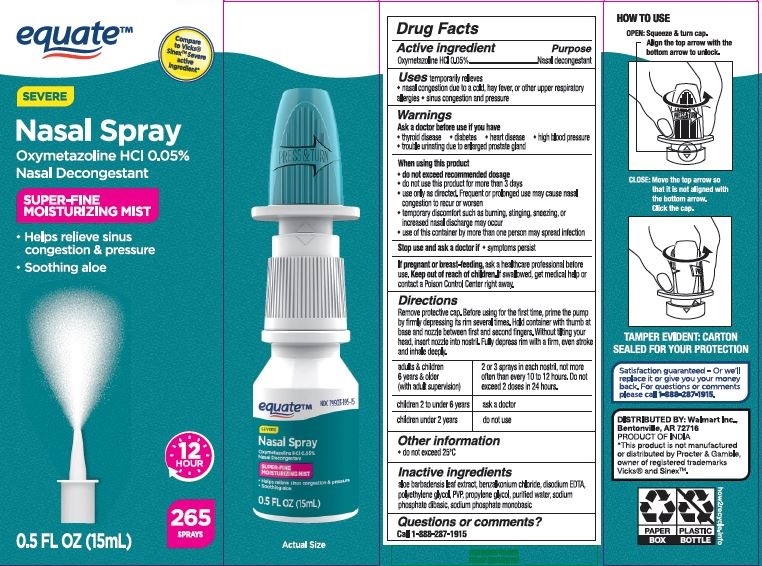 DRUG LABEL: Equate
NDC: 79903-346 | Form: SPRAY
Manufacturer: Walmart Inc
Category: otc | Type: HUMAN OTC DRUG LABEL
Date: 20260119

ACTIVE INGREDIENTS: OXYMETAZOLINE HYDROCHLORIDE 0.05 g/100 mL
INACTIVE INGREDIENTS: WATER; POVIDONE; PROPYLENE GLYCOL; SODIUM PHOSPHATE, DIBASIC; SODIUM PHOSPHATE, MONOBASIC; POLYETHYLENE GLYCOL, UNSPECIFIED; ALOE VERA LEAF; BENZYL ALCOHOL; BENZALKONIUM CHLORIDE; EDETATE DISODIUM

Equate Severe Nasal Spray

Active ingredients

Oxymetazoline HCL..........................0.05%

Purpose

Nasal decongestant

Uses

temporarily relieves

- nasal congestion due to a cold, hay fever, or other upper respiratory allergies
- sinus congestion and pressure

Warnings

For external use only;avoid contact with eyes. Do not use

- by mouth
- in nostrils
- on wounds or damaged skin
- with tight bandages

Ask a doctor before use if you have

- heart disease
- high blood pressure
- thyroid disease
- diabetes
- trouble urinating due to enlarged prostate gland

When using this product, do not

- do not exceed recommended dosage
- do not use this product for more than 3 days. Use only as directed. Frequent or prolonged use may cause nasal congestion to recur or worsen
- temporary discomfort such as burning, stinging, sneezing, or increased nasal discharge may occur
- use of this container by more than one person may spread infection

Stop use and ask a doctor if

- symptoms persist.

If pregnant or breast-feeding,

ask a health professional before use.

Keep out of reach of children.

If swallowed, get medical help or contact a Poison Control Center right away.

Directions

Remove protective cap. Before using for the first time, prime the pump by firmly depressing its rim several times. Hold container with thumb at base and nozzle between first and second fingers. Without tilting your head, insert nozzle into nostril. Fully depress rim with a firm, even stroke and inhale deeply.

- adults & children 6 yrs. & older (with adult supervision): 2 or 3 sprays in each nostril, not more often than every 10 to 12 hours. Do not exceed 2 doses in 24 hours.
- children 2 to under 6 yrs.: ask a doctor
- children under 2 yrs.: do not use

Other information

do not exceed 25°C

Inactive ingredients

aloe barbadensis leaf extract, benzalkonium chloride, disodium EDTA, polyethylene glycol, PVP, propylene glycol, purified water, sodium phosphate dibasic, sodium phosphate monobasic

Questions?

1-888-287-1915